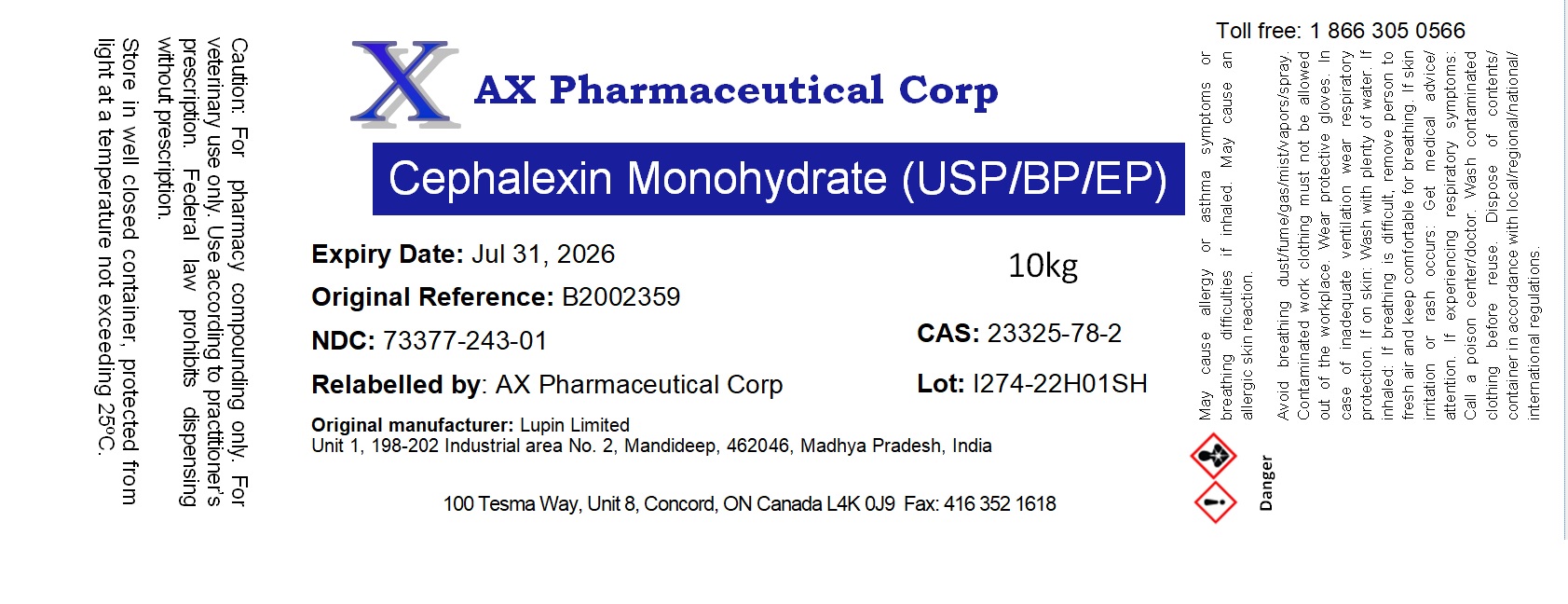 DRUG LABEL: Cephalexin Monohydrate
NDC: 73377-243 | Form: POWDER
Manufacturer: AX Pharmaceutical Corp
Category: other | Type: BULK INGREDIENT - ANIMAL DRUG
Date: 20231031

ACTIVE INGREDIENTS: CEPHALEXIN 1 g/1 g

Cephalexin Monohydrate